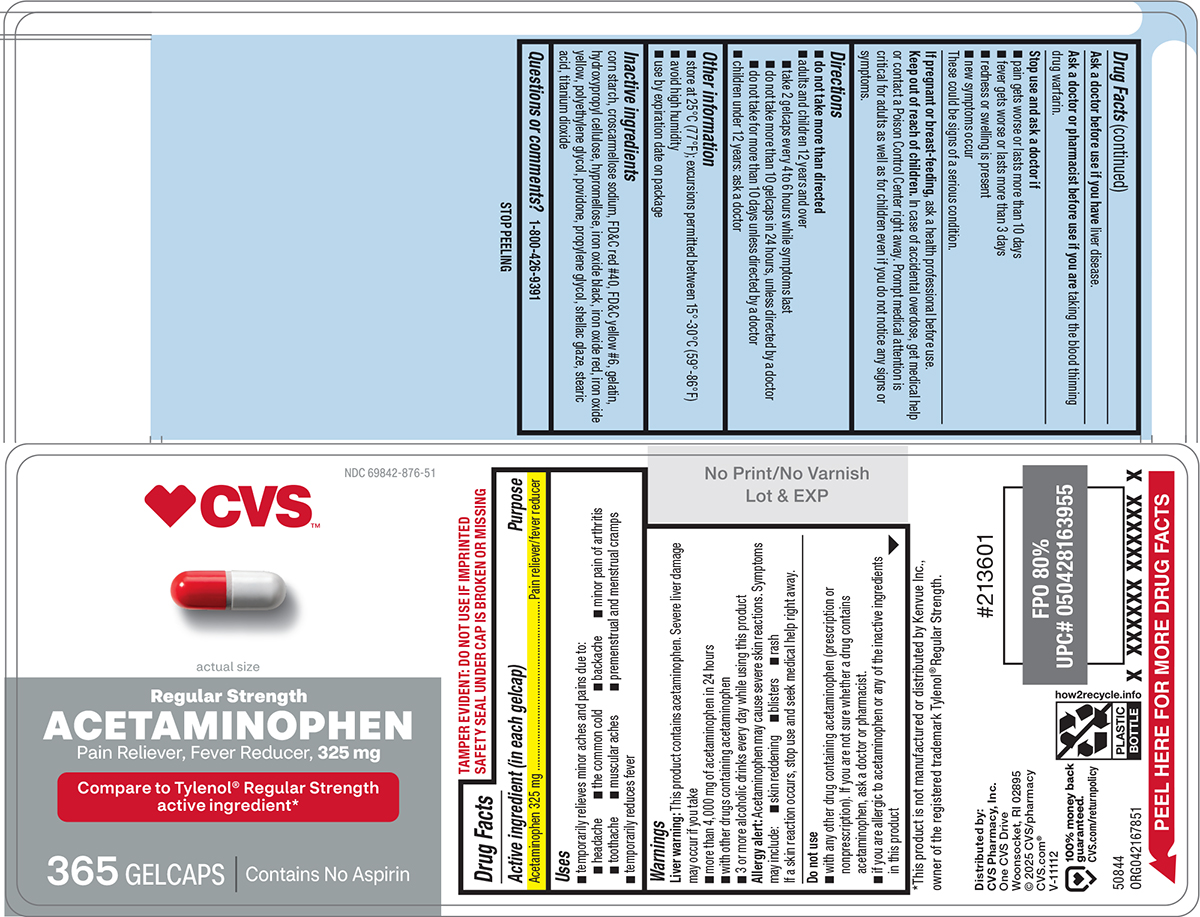 DRUG LABEL: Acetaminophen
NDC: 69842-876 | Form: TABLET, COATED
Manufacturer: CVS PHARMACY
Category: otc | Type: HUMAN OTC DRUG LABEL
Date: 20250421

ACTIVE INGREDIENTS: ACETAMINOPHEN 325 mg/1 1
INACTIVE INGREDIENTS: STARCH, CORN; CROSCARMELLOSE SODIUM; FD&C RED NO. 40; FD&C YELLOW NO. 6; GELATIN, UNSPECIFIED; HYDROXYPROPYL CELLULOSE, UNSPECIFIED; HYPROMELLOSE, UNSPECIFIED; FERROSOFERRIC OXIDE; FERRIC OXIDE RED; FERRIC OXIDE YELLOW; POLYETHYLENE GLYCOL, UNSPECIFIED; POVIDONE, UNSPECIFIED; PROPYLENE GLYCOL; SHELLAC; STEARIC ACID; TITANIUM DIOXIDE

CVS 44-678-Acetaminophen

Active ingredient (in each gelcap)

Acetaminophen 325 mg

Purpose

Pain reliever/fever reducer

Uses

- temporarily relieves minor aches and pains due to:
  - headache
  - the common cold
  - backache
  - minor pain of arthritis
  - toothache
  - muscular aches
  - premenstrual and menstrual cramps
- temporarily reduces fever

Warnings

Liver warning: This product contains acetaminophen. Severe liver damage may occur if you take

- more than 4,000 mg of acetaminophen in 24 hours
- with other drugs containing acetaminophen
- 3 or more alcoholic drinks every day while using this product

Allergy alert: Acetaminophen may cause severe skin reactions. Symptoms may include:

- skin reddening
- blisters
- rash

If a skin reaction occurs, stop use and seek medical help right away.

Do not use

- with any other drug containing acetaminophen (prescription or nonprescription). If you are not sure whether a drug contains acetaminophen, ask a doctor or pharmacist.
- if you are allergic to acetaminophen or any of the inactive ingredients in this product

Ask a doctor before use if you have

liver disease.

Ask a doctor or pharmacist before use if you are

taking the blood thinning drug warfarin.

Stop use and ask a doctor if

- pain gets worse or lasts more than 10 days
- fever gets worse or lasts more than 3 days
- new symptoms occur
- redness or swelling is present

These could be signs of a serious condition.

If pregnant or breast-feeding,

ask a health professional before use.

Keep out of reach of children.

In case of accidental overdose, get medical help or contact a Poison Control Center right away. Prompt medical attention is critical for adults as well as for children even if you do not notice any signs or symptoms.

Directions

- do not take more than directed
- adults and children 12 years and over
  - take 2 gelcaps every 4 to 6 hours while symptoms last
  - do not take more than 10 gelcaps in 24 hours, unless directed by a doctor
  - do not take for more than 10 days unless directed by a doctor
- children under 12 years: ask a doctor

Other information

- store at 25°C (77°F); excursions permitted between 15°-30°C (59°-86°F)
- avoid high humidity
- use by expiration date on package

Inactive ingredients

corn starch, croscarmellose sodium, FD&C red #40, FD&C yellow #6, gelatin, hydroxypropyl cellulose, hypromellose, iron oxide black, iron oxide red, iron oxide yellow, polyethylene glycol, povidone, propylene glycol, shellac glaze, stearic acid, titanium dioxide

Questions or comments?

1-800-426-9391

Principal display panel

CVS
Health™

NDC 69842-876-51

Regular Strength
Acetaminophen

Pain Reliever, Fever Reducer, 325 mg

Compare to Tylenol® Regular Strength
active ingredient*

actual size

365 GELCAPS

Contains No Aspirin

TAMPER EVIDENT: DO NOT USE IF IMPRINTED
SAFETY SEAL UNDER CAP IS BROKEN OR MISSING

This product is not manufactured or distributed by Kenvue Inc.,
owner of the registered trademark Tylenol® Regular Strength.
50844 ORG042167851

Distributed by:
CVS Pharmacy, Inc.
One CVS Drive
Woonsocket, RI 02895
© 2025 CVS/pharmacy
CVS.com®
V-11112

100% money back
guaranteed.
CVS.com/returnpolicy

CVS 44-678